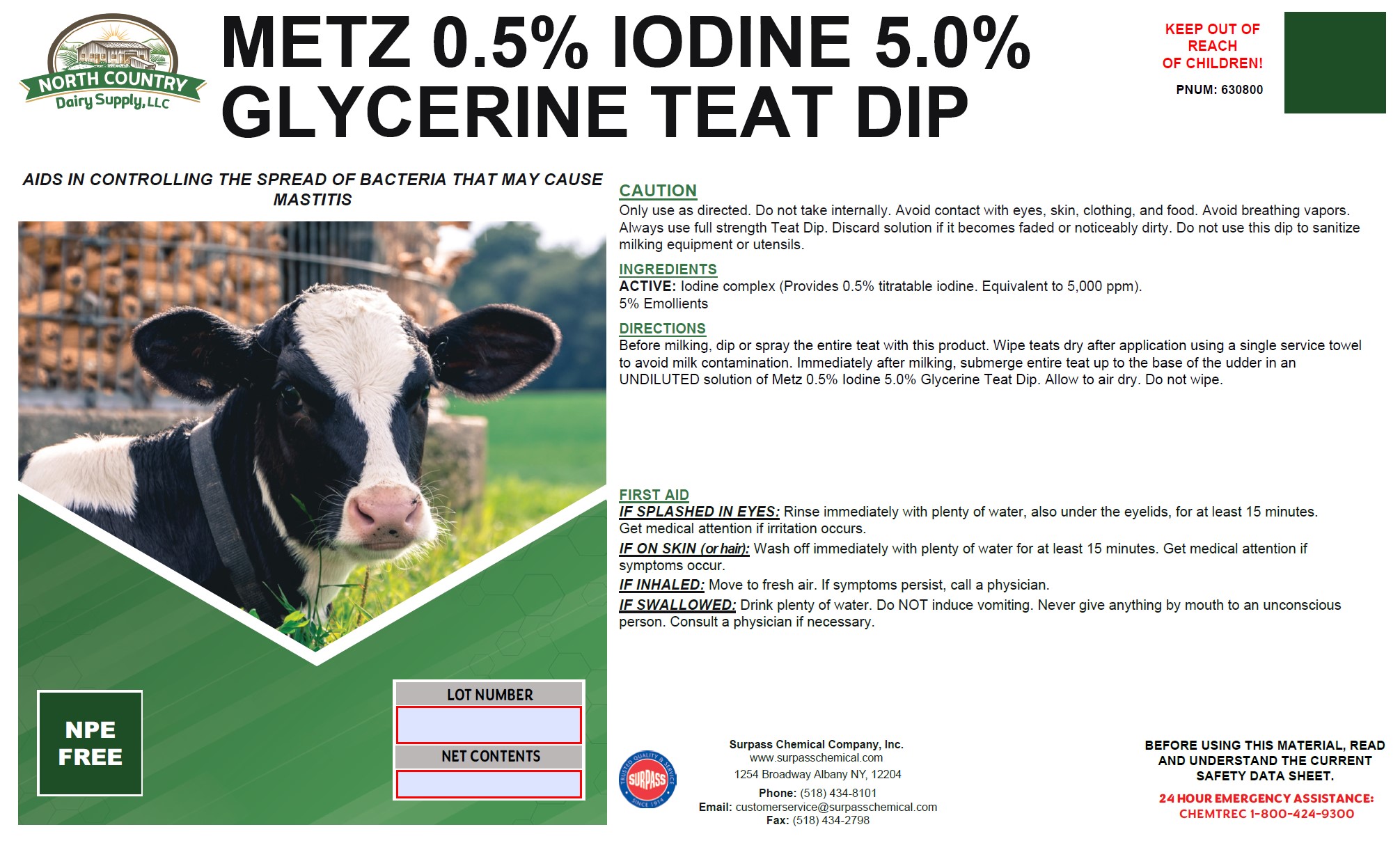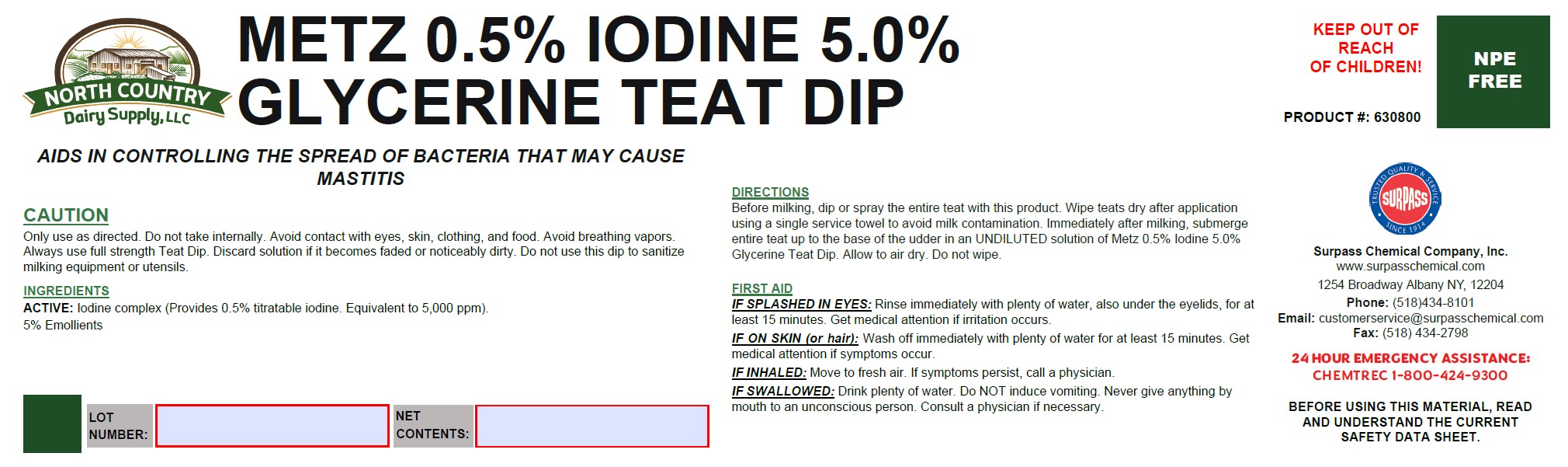 DRUG LABEL: Metz 0.5% Iodine 5.0% Glycerine Teat Dip
NDC: 86067-0124 | Form: SOLUTION
Manufacturer: Surpass Chemical. Company, Inc.
Category: animal | Type: OTC ANIMAL DRUG LABEL
Date: 20251229

ACTIVE INGREDIENTS: Iodine 0.0232 kg/1 kg
INACTIVE INGREDIENTS: WATER 0.8941 kg/1 kg; C9-11 PARETH-3 0.03 kg/1 kg; GLYCERIN 0.0487 kg/1 kg; TRISODIUM CITRATE DIHYDRATE 0.004 kg/1 kg

Metz 0.5% Iodine 5.0% Glycerine Teat Dip

DESCRIPTION

METZ 0.5% IODINE 5.0% GLYCERINE TEAT DIP

AIDS IN CONTROLLING THE SPREAD OF BACTERIA THAT MAY CAUSE MASTITIS PRODUCT #: 630800

DIRECTIONS:
Before milking, dip or spray the entire teat with this product. Wipe teats dry after application using a single service towerl to avoid milk contamination. Immediately after milking, submerge entire teat up to the base of the udder in an UNDIULUTED solution of 0.5% Iodine 5.0% Glycerine Teat Dip. Allow to air dry. Do not wipe.

GENERAL PRECAUTIONS

CAUTION:
Only use as directed. Do not take internally. Avoid contact with eyes, skin, clothing, and food. Avoid breathing vapors. Discard
solution if it becomes faded or noticeably dirty. Do not use to sanitize milking equipment or utensils.

ACTIVE INGREDIENT

INGREDIENTS:
ACTIVE: Iodine complex (Provides 0.5% titratable iodine. Equivalent to 5,000 ppm).

5% Emollients

OTHER SAFETY INFORMATION

FIRST AID:

IF SPLASHED IN EYES:Rinse immediately with plenty of water, also under the eyelids, for at least 15 minutes.Get medical attention irritation occurs.

If ON SKIN (or hair):Wash off immediately with soap and plenty of water while removing all contaminated clothes and shoes. Get medical attention if symptons occur.

IF INHALED:Move to fresh air. If symptons persist, call a physician.

IF SWALLOWED: Drink plenty of water. Do NOT induce vomiting. Never give anything by mouth to an unconcious person. Consult a physician if necessary.

KEEP OUT OF REACH OF CHILDREN!

Surpass Chemical Company, Inc. Phone: (518) 434-8101 24 HOUR EMERGENCY SERVICE

www.surpasschemical.com Email: (518) 434-2798 CHEMTREC 1-800-424-9300

1254 Broadway Albany NY 12204 Email: customerservice@surpasschemical.com KEEP OUT OF REACH OF CHILDREN